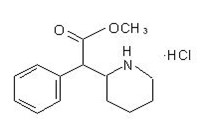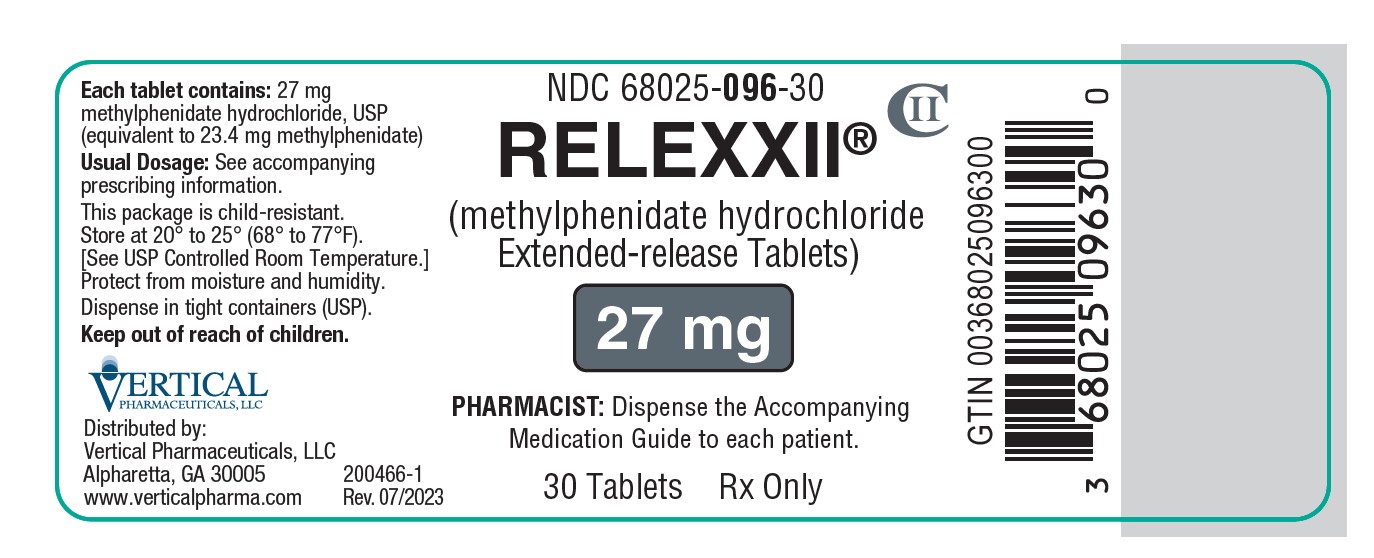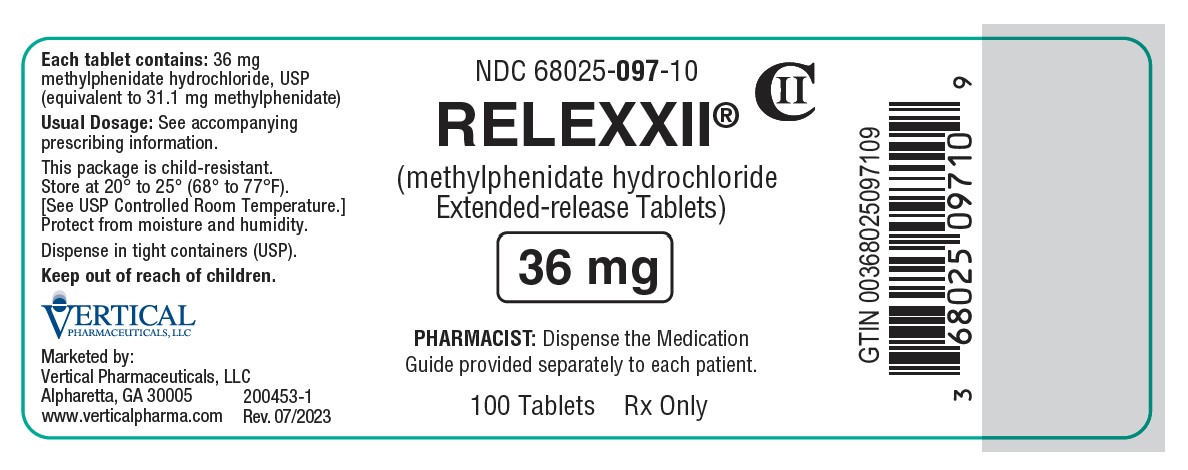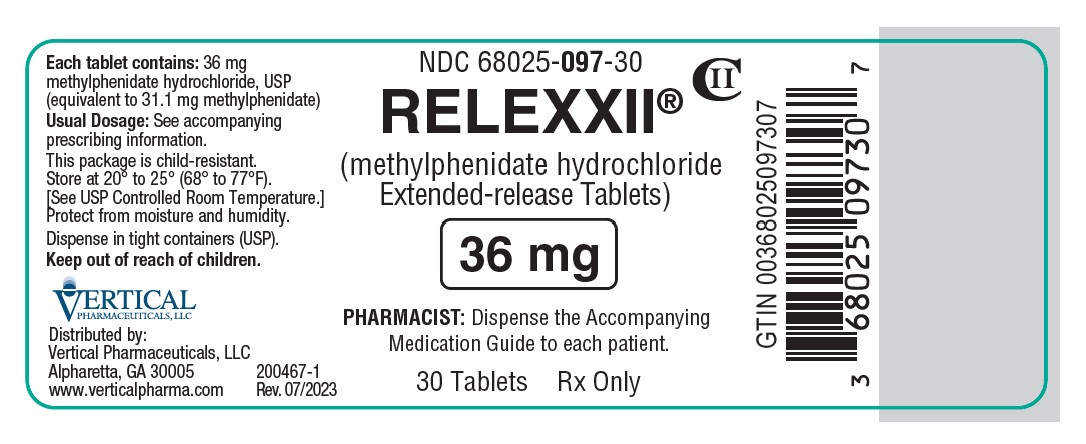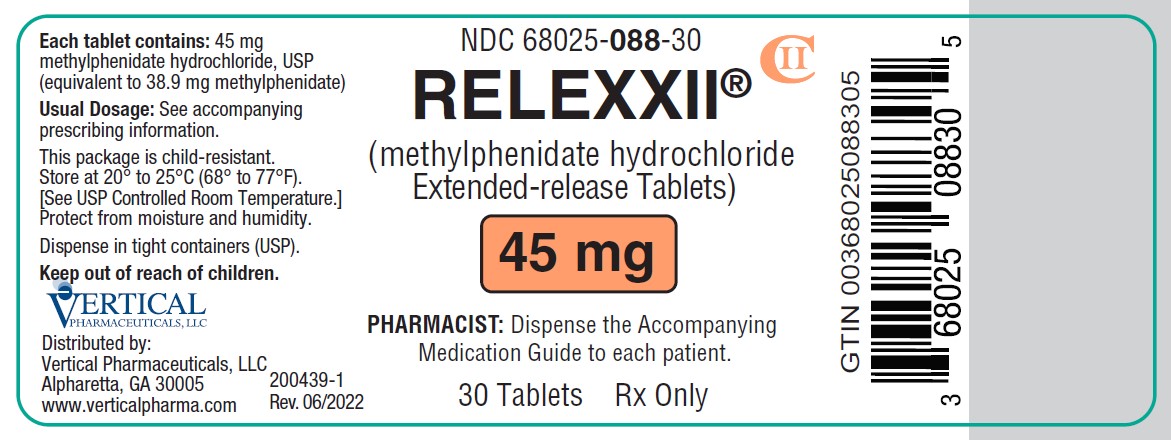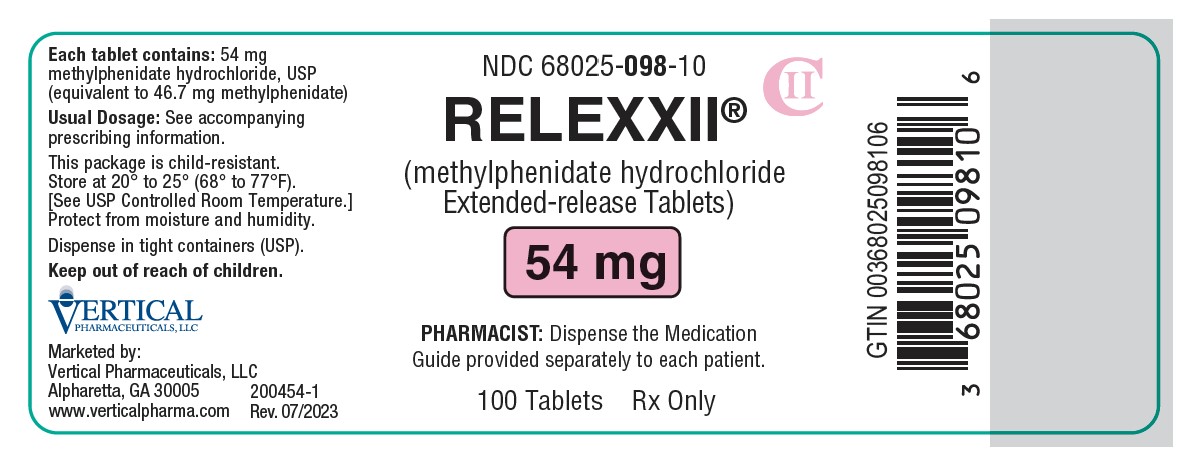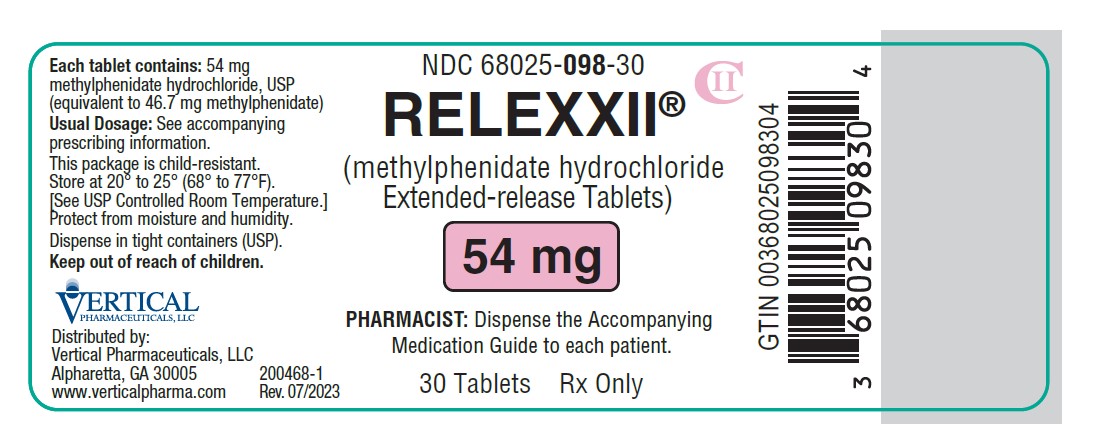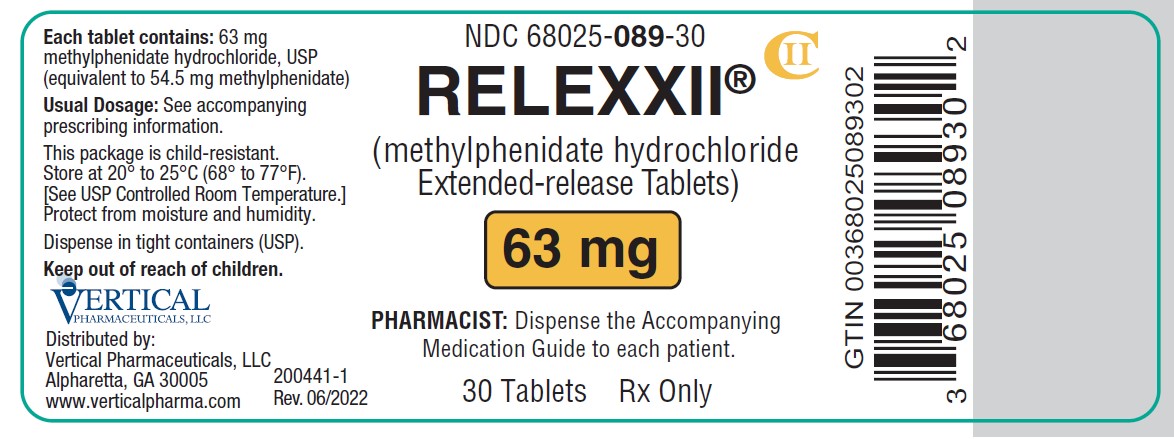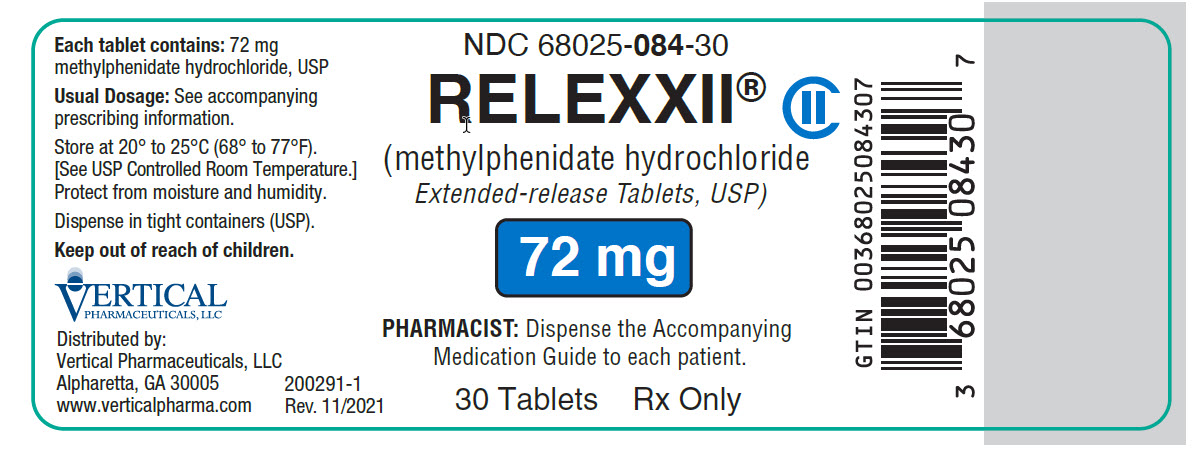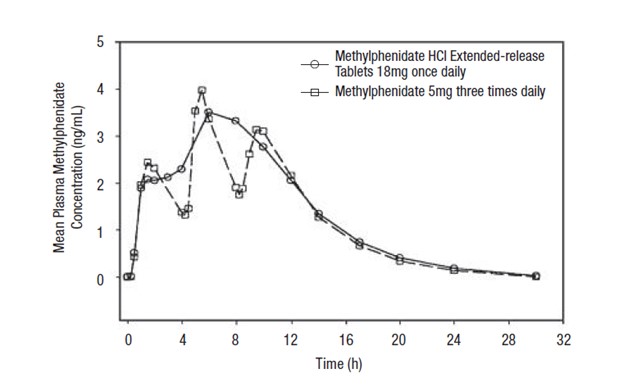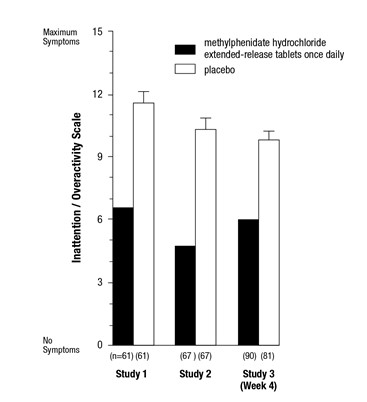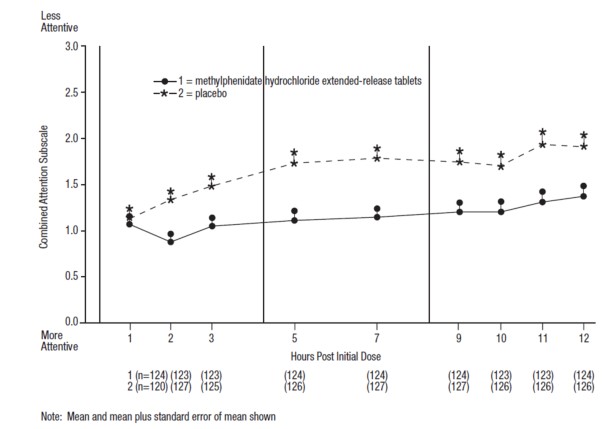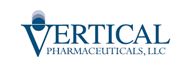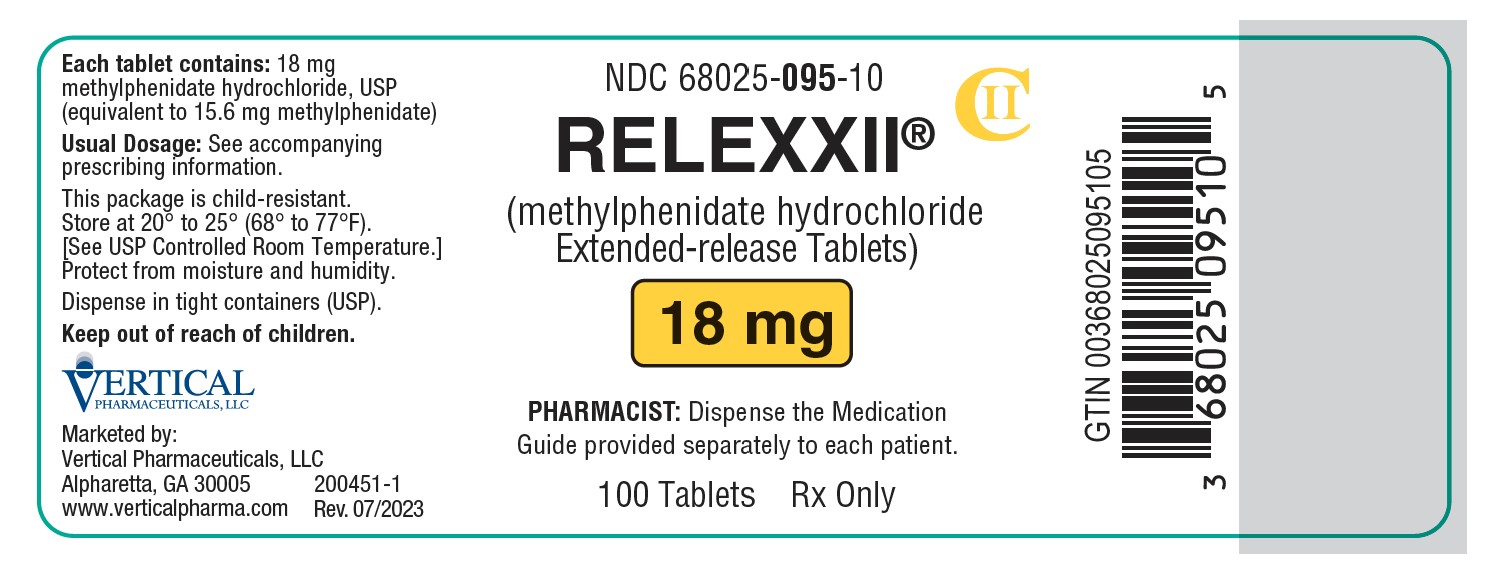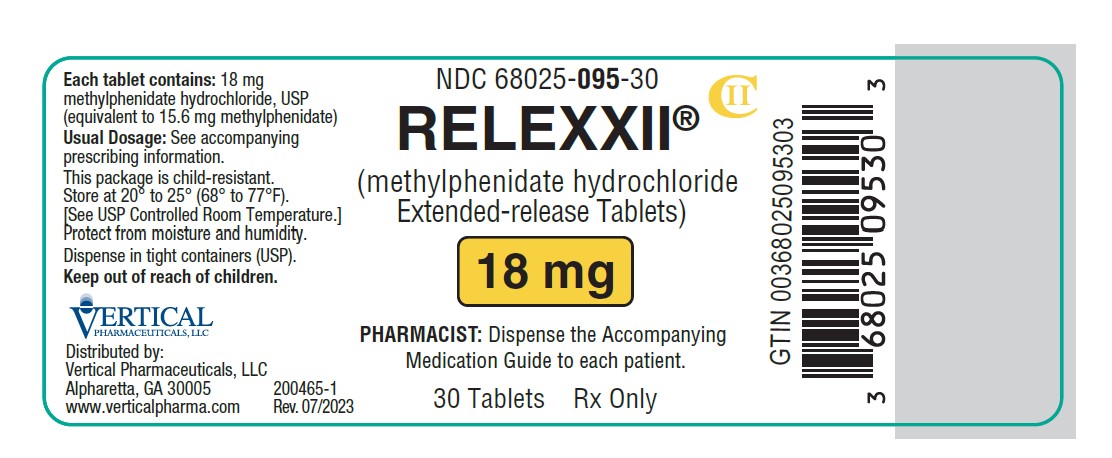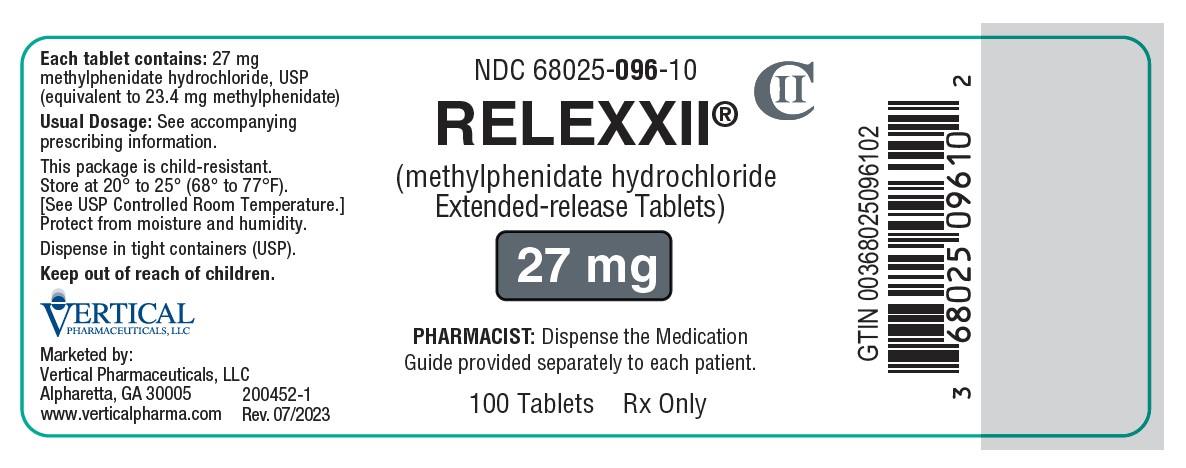 DRUG LABEL: RELEXXII
NDC: 68025-088 | Form: TABLET, EXTENDED RELEASE
Manufacturer: Vertical Pharmaceuticals, LLC
Category: prescription | Type: HUMAN PRESCRIPTION DRUG LABEL
Date: 20250926
DEA Schedule: CII

ACTIVE INGREDIENTS: METHYLPHENIDATE HYDROCHLORIDE 45 mg/1 1
INACTIVE INGREDIENTS: HYPROMELLOSES; PHOSPHORIC ACID; POLYETHYLENE GLYCOL, UNSPECIFIED; SILICON DIOXIDE; SODIUM CHLORIDE; MAGNESIUM STEARATE; SUCCINIC ACID; FERROSOFERRIC OXIDE; TITANIUM DIOXIDE; FD&C RED NO. 40; CELLULOSE ACETATE; LACTOSE MONOHYDRATE; POLYETHYLENE OXIDE 200000; POLYETHYLENE OXIDE 5000000; TRIACETIN

HIGHLIGHTS OF PRESCRIBING INFORMATION

These highlights do not include all the information needed to use RELEXXII® safely and effectively. See full prescribing information for RELEXXII®.
RELEXXII® (methylphenidate hydrochloride extended-release tablets) for oral use, CII
Initial U.S. Approval: 2000

WARNING: ABUSE, MISUSE, AND ADDICTION

See full prescribing information for complete boxed warning.

RELEXXII has a high potential for abuse and misuse, which can lead to the development of a substance use disorder, including addiction. Misuse and abuse of CNS stimulants, including RELEXXII, can result in overdose and death (5.1, 9.2, 10):

- Before prescribing RELEXXII, assess each patient’s risk for abuse, misuse, and addiction.
- Educate patients and their families about these risks, proper storage of the drug, and proper disposal of any unused drug.
- Throughout treatment, reassess each patient’s risk and frequently monitor for signs and symptoms of abuse, misuse, and addiction.

RECENT MAJOR CHANGES

Indications and Usage (1) 09/2025

Warnings and Precautions (5.7) 09/2025

1 INDICATIONS AND USAGE

RELEXXII® is a central nervous system (CNS) stimulant indicated for the treatment of Attention Deficit Hyperactivity Disorder (ADHD) in adults (up to the age of 65 years) and pediatric patients 6 years of age and older (1).

Limitations of Use

The use of RELEXXII is not recommended in pediatric patients younger than 6 years of age because they had higher plasma exposure and a higher incidence of adverse reactions (e.g., weight loss) than patients 6 years and older at the same dosage (5.7, 8.4).

2 DOSAGE AND ADMINISTRATION

- Administer once daily in the morning with or without food. (2.2)
- Swallow whole with liquid. Do not chew, divide, or crush. (2.2)
- Recommended dosage for patients new to methylphenidate (2.3):

- Pediatric patients 6 to 17 years
  - Starting dosage is 18 mg once daily. Dosage may be increased by 18 mg once per day at weekly intervals.
  - Maximum dosage for pediatric patients 6 to 12 years: 54 mg once daily.
  - Maximum dosage for pediatric patients 13 to 17 years: 72 mg once daily.
- Adults (up to 65 years)
  - Starting dosage is 18 mg or 36 mg once daily. Dosage may be increased by 18 mg once daily at weekly intervals.
  - Maximum dosage: 72 mg once daily.

3 DOSAGE FORMS AND STRENGTHS

Extended-release tablets:18 mg, 27 mg, 36 mg, 45 mg, 54 mg, 63 mg, and 72 mg (3)

4 CONTRAINDICATIONS

- Known hypersensitivity to methylphenidate or other components of RELEXXII (4)
- Concurrent treatment with a monoamine oxidase inhibitor (MAOI), or use of an MAOI within the preceding 14 days (4)

5 WARNINGS AND PRECAUTIONS

- Risks to Patients with Serious Cardiac Disease: Avoid use in patients with known structural cardiac abnormalities, cardiomyopathy, serious cardiac arrhythmias, coronary artery disease, or serious cardiac disease. (5.2)
- Increased Blood Pressure and Heart Rate: Monitor blood pressure and pulse. (5.3)

- Psychiatric Adverse Reactions: Prior to initiating RELEXXII, screen patients for risk factors for developing a manic episode. If new psychotic or manic symptoms occur, consider discontinuing RELEXXII. (5.4)
- Priapism: If abnormally sustained or frequent and painful erections occur, patients should seek immediate medical attention. (5.5)
- Peripheral Vasculopathy, including Raynaud’s Phenomenon: Careful observation for digital changes is necessary during RELEXXII treatment. Further clinical evaluation (e.g., rheumatology referral) may be appropriate for patients who develop signs or symptoms of peripheral vasculopathy. (5.6)
- Long-Term Suppression of Growth in Pediatric Patients: Closely monitor growth (height and weight) in pediatric patients. Pediatric patients not growing or gaining weight as expected may need to have their treatment interrupted. (5.7)
- Gastrointestinal Obstruction: Avoid use with preexisting GI narrowing. (5.8)
- Acute Angle Closure Glaucoma: RELEXXII-treated patients considered at risk for acute angle closure glaucoma (e.g., patients with significant hyperopia) should be evaluated by an ophthalmologist. (5.9)
- Increased Intraocular Pressure (IOP) and Glaucoma: Prescribe RELEXXII to patients with open-angle glaucoma or abnormally increased IOP only if the benefit of treatment is considered to outweigh the risk. Closely monitor patients with a history of increased IOP or open angle glaucoma. (5.10)
- Motor and Verbal Tics, and Worsening of Tourette’s Syndrome: Before initiating RELEXXII, assess the family history and clinically evaluate patients for tics or Tourette’s syndrome. Regularly monitor patients for the emergence or worsening of tics or Tourette’s syndrome. Discontinue treatment if clinically appropriate. (5.11)

6 ADVERSE REACTIONS

The most common adverse reactions (>5%) were:

Pediatric patients 6 to 17 years: abdominal pain upper (6.1)

Adults: decreased appetite, headache, dry mouth, nausea, insomnia, anxiety, dizziness, weight decreased, irritability, and hyperhidrosis (6.1)

To report SUSPECTED ADVERSE REACTIONS, contact Vertical Pharmaceuticals, LLC at 1-800-444-5164 or FDA at 1-800-FDA-1088 or www.fda.gov/medwatch.

7 DRUG INTERACTIONS

Antihypertensive Drugs: Monitor blood pressure. Adjust dosage of antihypertensive drug as needed (7.1)

FULL PRESCRIBING INFORMATION

WARNING: ABUSE, MISUSE, AND ADDICTION

RELEXXII has a high potential for abuse and misuse, which can lead to the development of a substance use disorder, including addiction. Misuse and abuse of CNS stimulants, including RELEXXII, can result in overdose and death [see Overdosage (10)], and this risk is increased with higher doses or unapproved methods of administration, such as snorting or injection.

Before prescribing RELEXXII, assess each patient’s risk for abuse, misuse, and addiction. Educate patients and their families about these risks, proper storage of the drug, and proper disposal of any unused drug. Throughout RELEXXII treatment, reassess each patient’s risk of abuse, misuse, and addiction and frequently monitor for signs and symptoms of abuse, misuse, and addiction [see Warnings and Precautions (5.1) and Drug Abuse and Dependence (9.2)].

1 INDICATIONS AND USAGE

RELEXXII is indicated for the treatment of Attention Deficit Hyperactivity Disorder (ADHD) in adults (up to the age of 65 years) and pediatric patients 6 years of age and older [see Clinical Studies (14)].

Limitations of Use

The use of RELEXXII is not recommended in pediatric patients younger than 6 years of age because they had higher plasma exposure and a higher incidence of adverse reactions (e.g., weight loss) than patients 6 years and older at the same dosage [see Warnings and Precautions (5.7), Use in Specific Populations (8.4)].

2 DOSAGE AND ADMINISTRATION

2.1 Pretreatment Screening

Prior to treating patients with RELEXXII, assess:

- for the presence of cardiac disease (i.e., perform a careful history, family history of sudden death or ventricular arrhythmia, and physical exam) [see Warnings and Precautions (5.2)].
- the family history and clinically evaluate patients for motor or verbal tics or Tourette’s syndrome before initiating RELEXXII [see Warnings and Precautions (5.11)].

2.2 General Administration Information

Administer RELEXXII orally once daily in the morning with or without food.

Swallow RELEXXII whole with liquid. Do not chew, divide, or crush [see Warnings and Precautions (5.8)].

2.3 Dosage Recommendations for Patients New to Methylphenidate

Table 1 includes the starting dosage and dosage recommendations for RELEXXII in pediatric patients 6 to 17 years and adults who are not currently taking methylphenidate or other stimulants.

Table 1: Dosage Recommendations for RELEXXII in Pediatric Patients 6 to 17 years and Adults

Patient Population | RELEXXII Recommended Starting Dosage | RELEXXII Dosage Range
Pediatric patients; 6 to 12 years | 18 mg once daily | 18 mg to 54 mg once daily
13 to 17 years | 18 mg once daily | 18 mg to 72 mg once daily; (not to exceed 2 mg/kg/day)
Adults; 18 (up to 65 years) | 18 mg or 36 mg once daily | 18 mg to 72 mg once daily

2.4 Dosage Recommendations for Patients Currently Using Methylphenidate

The recommended starting dosage of RELEXXII for patients who are currently taking methylphenidate twice daily or three times daily at doses of 10 mg to 60 mg daily is provided in Table 2.

Table 2: Recommended Starting Dosage when Converting from Methylphenidate Regimens to RELEXXII

Current Methylphenidate Daily Dosage | Recommended Starting Dosage of RELEXXII
5 mg methylphenidate twice daily or three times daily | 18 mg once daily in the morning
10 mg methylphenidate twice daily or three times daily | 36 mg once daily in the morning
15 mg methylphenidate twice daily or three times daily | 54 mg once daily in the morning
20 mg methylphenidate twice daily or three times daily | 72 mg once daily in the morning

2.5 Dose Titration

Doses may be increased in 18 mg increments at weekly intervals for patients who have not achieved clinical response at a lower dose. Daily dosages above 54 mg in pediatric patients 6 to 12 years and above 72 mg in pediatric patients 13 to 17 years have not been studied and are not recommended. Daily dosages above 72 mg are not recommended in adults.

Dosage strengths of 27 mg, 45 mg, and 63 mg are available for additional titration options based on clinical response.

2.6 Dosage Reduction and Discontinuation

If paradoxical aggravation of symptoms or other adverse reaction occur, reduce the dosage, or, if necessary, discontinue RELEXXII.

If improvement is not observed after appropriate dosage adjustment over a one-month period, discontinue RELEXXII.

3 DOSAGE FORMS AND STRENGTHS

RELEXXII (methylphenidate hydrochloride extended-release tablets) are available in the following strengths:

- 18 mg: yellow with “TL706” imprinted in black ink
- 27 mg: gray with “TL707” imprinted in black ink
- 36 mg: white with “TL708” imprinted in black ink
- 45 mg: pink with “TL711” imprinted in black ink
- 54 mg: pink with “TL709” imprinted in black ink
- 63 mg: orange with “TL700” imprinted in black ink and
- 72 mg: blue with “TL710” imprinted in black ink.

4 CONTRAINDICATIONS

RELEXXII is contraindicated in patients:

- with a known hypersensitivity to methylphenidate or other components of RELEXXII. Hypersensitivity reactions such as angioedema and anaphylactic reactions have been reported in patients treated with other methylphenidate products [see Adverse Reactions (6.2)].
- receiving concomitant treatment with monoamine oxidase inhibitors (MAOIs), and also within 14 days following discontinuation of treatment with a MAOI, because of the risk of hypertensive crisis [see Drug Interactions (7.1)].

5 WARNINGS AND PRECAUTIONS

5.1 Abuse, Misuse, and Addiction

RELEXXII has a high potential for abuse and misuse. The use of RELEXXII exposes individuals to the risks of abuse and misuse, which can lead to the development of a substance use disorder, including addiction. RELEXXII can be diverted for non-medical use into illicit channels or distribution [see Drug Abuse and Dependence (9.2, 9.3)]. Misuse and abuse of CNS stimulants, including RELEXXII, can result in overdose and death [see Overdosage (10)], and this risk is increased with higher doses or unapproved methods of administration, such as snorting or injection.

Before prescribing RELEXXII, assess each patient’s risk for abuse, misuse, and addiction. Educate patients and their families about these risks and proper disposal of any unused drug. Advise patients to store RELEXXII in a safe place, preferably locked, and instruct patients to not give RELEXXII to anyone else. Throughout RELEXXII treatment, reassess each patient’s risk of abuse, misuse, and addiction and frequently monitor for signs and symptoms of abuse, misuse, and addiction.

5.2 Risks to Patients with Serious Cardiac Disease

Sudden death has been reported in patients with structural cardiac abnormalities or other serious cardiac disease who were taking CNS stimulants at the recommended ADHD dosage. Avoid RELEXXII use in patients with known structural cardiac abnormalities, cardiomyopathy, serious cardiac arrhythmia, coronary artery disease, or other serious cardiac disease.

5.3 Increased Blood Pressure and Heart Rate

CNS stimulants cause an increase in blood pressure (mean increase approximately 2 to 4 mm Hg) and heart rate (mean increase approximately 3 to 6 bpm) [see Adverse Reactions (6.1)]. Some patients may have larger increases. Monitor all RELEXXII-treated patients for hypertension and tachycardia.

5.4 Psychiatric Adverse Reactions

Exacerbation of Pre-existing Psychosis

CNS stimulants may exacerbate symptoms of behavior disturbance and thought disorder in patients with a preexisting psychotic disorder.

Induction of a Manic Episode in Patients with Bipolar Disorder

CNS stimulants may induce a manic or mixed episode in patients. Prior to initiating RELEXXII treatment, screen patients for risk factors for developing a manic episode (e.g., comorbid or history of depressive symptoms, a family history of suicide, bipolar disorder, and depression).

New Psychotic or Manic Symptoms

CNS stimulants, at the recommended dosage, may cause psychotic or manic symptoms (e.g., hallucinations, delusional thinking, or mania) in patients without a prior history of psychotic illness or mania. In a pooled analysis of multiple short-term, placebo-controlled studies of CNS stimulants, psychotic or manic, symptoms occurred in approximately 0.1% of CNS stimulant-treated patients compared to 0% of placebo-treated patients. If such symptoms occur, consider discontinuing RELEXXII.

5.5 Priapism

Prolonged and painful erections, sometimes requiring surgical intervention, have been reported with methylphenidate use, including another formulation of methylphenidate hydrochloride extended-release tablets, in both adult and pediatric male patients [see Adverse Reactions (6.2)]. Although priapism was not reported with methylphenidate initiation, it developed after some time on methylphenidate, often subsequent to an increase in dosage. Priapism also occurred during a methylphenidate withdrawal (drug holidays or during discontinuation).

RELEXXII-treated patients who develop abnormally sustained or frequent and painful erections should seek immediate medical attention.

5.6 Peripheral Vasculopathy, including Raynaud’s Phenomenon

CNS stimulants, such as RELEXXII, used to treat ADHD are associated with peripheral vasculopathy, including Raynaud’s phenomenon. Signs and symptoms are usually intermittent and mild; however, sequelae have included digital ulceration and/or soft tissue breakdown. Effects of peripheral vasculopathy, including Raynaud’s phenomenon, were observed in post-marketing reports and at the therapeutic dosage in all age groups throughout the course of treatment. Signs and symptoms generally improved after reduction or discontinuation of the CNS stimulant.

Careful observation for digital changes is necessary during RELEXXII treatment. Further clinical evaluation (e.g., rheumatology referral) may be appropriate for RELEXXII-treated patients who develop signs or symptoms of peripheral vasculopathy.

5.7 Long-Term Suppression of Growth in Pediatric Patients

RELEXXII is not approved for use and is not recommended in pediatric patients below 6 years of age [see Use in Specific Populations (8.4)].

CNS stimulants have been associated with weight loss and slowing of growth rate in pediatric patients.

Careful follow-up of weight and height in pediatric patients ages 7 to 10 years who were randomized to either methylphenidate or nonmedication treatment groups over 14 months, as well as in naturalistic subgroups of newly methylphenidate-treated and nonmedication-treated pediatric patients over 36 months (to the ages of 10 to 13 years), suggests that pediatric patients who received methylphenidate for 7 days per week throughout the year had a temporary slowing in growth rate (on average, a total of about 2 cm less growth in height and 2.7 kg less growth in weight over 3 years), without evidence of growth rebound during this development period.

Closely monitor growth (weight and height) in RELEXXII-treated pediatric patients. Pediatric patients who are not growing or gaining height or weight as expected may need to have their treatment interrupted.

5.8 Potential for Gastrointestinal Obstruction

Because the RELEXXII tablet is nondeformable and does not appreciably change in shape in the GI tract, RELEXXII should not ordinarily be administered to patients with preexisting severe gastrointestinal narrowing (pathologic or iatrogenic, for example: esophageal motility disorders, small bowel inflammatory disease, "short gut" syndrome due to adhesions or decreased transit time, past history of peritonitis, cystic fibrosis, chronic intestinal pseudo-obstruction, or Meckel's diverticulum). There have been rare reports of obstructive symptoms in patients with known strictures in association with the ingestion of drugs in nondeformable controlled-release formulations. Due to the extended-release design of the tablet, RELEXXII should be used only in patients who are able to swallow the tablet whole [see Patient Counseling Information (17)].

5.9 Acute Angle Closure Glaucoma

There have been reports of angle closure glaucoma associated with methylphenidate treatment. Although the mechanism is not clear, RELEXXII-treated patients considered at risk for acute angle closure glaucoma (e.g., patients with significant hyperopia) should be evaluated by an ophthalmologist.

5.10 Increased Intraocular Pressure and Glaucoma

There have been reports of an elevation of intraocular pressure (IOP) associated with methylphenidate treatment [see Adverse Reactions (6.2)].

Prescribe RELEXXII to patients with open-angle glaucoma or abnormally increased IOP only if the benefit of treatment is considered to outweigh the risk. Closely monitor RELEXXII-treated patients with a history of abnormally increased IOP or open angle glaucoma.

5.11 Motor and Verbal Tics, and Worsening of Tourette's Syndrome

CNS stimulants, including methylphenidate, have been associated with the onset or exacerbation of motor and verbal tics. Worsening of Tourette’s syndrome has also been reported [see Adverse Reactions (6.2)].

Before initiating RELEXXII, assess the family history and clinically evaluate patients for tics or Tourette’s syndrome. Regularly monitor RELEXXII-treated patients for the emergence or worsening of tics or Tourette’s syndrome, and discontinue treatment if clinically appropriate.

6 ADVERSE REACTIONS

The following are discussed in more detail in other sections of the labeling:

- Abuse, Misuse, and Addiction [see Box Warning, Warnings and Precautions (5.1), and Drug Abuse and Dependence (9.2, 9.3)]
- Known hypersensitivity to methylphenidate or other ingredients [see Contraindications (4)]
- Hypertensive crisis when used concomitantly with monoamine oxidase inhibitors [see Contraindications (4) and Drug Interactions (7.1)]
- Risks to Patients with Serious Cardiac Disease [see Warnings and Precautions (5.2)]
- Increased Blood Pressure and Heart Rate [see Warnings and Precautions (5.3)]
- Psychiatric Adverse Reactions [see Warnings and Precautions (5.4)]
- Priapism [see Warnings and Precautions (5.5)]
- Peripheral Vasculopathy, including Raynaud’s Phenomenon [see Warnings and Precautions (5.6)]
- Long-Term Suppression of Growth in Pediatric Patients [see Warnings and Precautions (5.7)]
- Potential for Gastrointestinal Obstruction [see Warnings and Precautions (5.8)]
- Acute Angle Closure Glaucoma [see Warnings and Precautions (5.9)]
- Increased Intraocular Pressure and Glaucoma [see Warnings and Precautions (5.10)]
- Motor and Verbal Tics, and Worsening of Tourette’s Syndrome [see Warnings and Precautions (5.11)]

6.1 Clinical Trials Experience

Because clinical trials are conducted under widely varying conditions, adverse reaction rates observed in the clinical trials of a drug cannot be directly compared to rates in clinical trials of another drug and may not reflect the rates observed in clinical practice.

The safety of RELEXXII for the treatment of ADHD is based on adequate and well-controlled studies of another formulation of methylphenidate hydrochloride extended-release tablets. Below is a display of adverse reactions from those adequate and well-controlled studies in ADHD.

Adults and pediatric patients 6 to 17 years with ADHD were evaluated in six controlled clinical studies and eleven open-label clinical studies (see Table 3). Safety was assessed by collecting adverse reactions, vital signs, weights, and electrocardiograms (ECGs), and by performing physical examinations and laboratory analyses. A total of 3,906 patients participated in the clinical trials.

Table 3: Exposure in Double-Blind and Open-Label Clinical Studies of Another Formulation of Methylphenidate Hydrochloride Extended-Release Tablets

Patient Population | N | Dosage Range
Pediatric patients 6 to 12 years | 2216 | 18 mg to 54 mg once daily
Pediatric patients 13 to 17 years | 502 | 18 mg to 72 mg once daily
Adults | 1188 | 18 mg to 108 mg* once daily

* 108 mg is 1.5 times the maximum recommended dosage of RELEXXII.

The most common adverse reactions in double-blind clinical trials (>5%) were:

- Pediatric patients 6 to 17 years: abdominal pain upper (see Table 4).
- Adults: decreased appetite, headache, dry mouth, nausea, insomnia, anxiety, dizziness, weight decreased, irritability, and hyperhidrosis (see Table 5).

The most common adverse reactions associated with discontinuation (≥1%) from either pediatric or adult clinical trials were anxiety, irritability, insomnia, and blood pressure increased.

Adverse reactions in either the pediatric or adult double-blind adverse reactions tables may be relevant for both patient populations.

Pediatric Patients 6 to 17 Years

Table 4 lists the adverse reactions reported in 1% or more of another formulation of methylphenidate hydrochloride extended-release tablet-treated pediatric patients (6 to 17 years) in four placebo-controlled, double-blind clinical trials.

Table 4: Adverse Reactions Reported by ≥1% of Pediatric Patients (6 to 17 years) Treated with Another Formulation of Methylphenidate Hydrochloride Extended-release Tablets in Four Placebo-Controlled, Double-Blind Clinical Trials

System/Organ Class Adverse Reaction | Another Formulation of Methylphenidate Hydrochloride Extended-release Tablets (n=321) % | Placebo (n=318) %
Gastrointestinal Disorders
Abdominal pain upper | 6.2 | 3.8
Vomiting | 2.8 | 1.6
General Disorders and Administration Site Conditions
Pyrexia | 2.2 | 0.9
Infections and Infestations
Nasopharyngitis | 2.8 | 2.2
Nervous System Disorders
Dizziness | 1.9 | 0
Psychiatric Disorders
Insomnia* | 2.8 | 0.3
Respiratory, Thoracic and Mediastinal Disorders
Cough | 1.9 | 0.9
Oropharyngeal pain | 1.2 | 0.9
* Terms of Initial insomnia (methylphenidate hydrochloride extended-release tablets =0.6%) and Insomnia (methylphenidate hydrochloride extended-release tablets =2.2%) are combined into Insomnia.

Adults

Table 5 lists the adverse reactions reported in 1% or more of adults treated with another formulation of methylphenidate hydrochloride extended-release tablets in two placebo-controlled, double-blind clinical trials.

Table 5: Adverse Reactions Reported by ≥1% of Adults Treated with Another Formulation of Methylphenidate Hydrochloride Extended-release Tablets in Two Placebo-Controlled, Double-Blind Clinical Trials*

System/Organ Class Adverse Reaction | Another Formulation of Methylphenidate Hydrochloride Extended-release Tablets (n=415) % | Placebo (n=212) %
Cardiac Disorders
Tachycardia | 4.8 | 0
Palpitations | 3.1 | 0.9
Ear and Labyrinth Disorders
Vertigo | 1.7 | 0
Eye Disorders
Vision blurred | 1.7 | 0.5
Gastrointestinal Disorders
Dry mouth | 14.0 | 3.8
Nausea | 12.8 | 3.3
Dyspepsia | 2.2 | 0.9
Vomiting | 1.7 | 0.5
Constipation | 1.4 | 0.9
General Disorders and Administration Site Conditions
Irritability | 5.8 | 1.4
Infections and Infestations
Upper respiratory tract infection | 2.2 | 0.9
Investigations
Weight decreased | 6.5 | 3.3
Metabolism and Nutrition Disorders
Decreased appetite | 25.3 | 6.6
Anorexia | 1.7 | 0
Musculoskeletal and Connective Tissue Disorders
Muscle tightness | 1.9 | 0
Nervous System Disorders
Headache | 22.2 | 15.6
Dizziness | 6.7 | 5.2
Tremor | 2.7 | 0.5
Paresthesia | 1.2 | 0
Sedation | 1.2 | 0
Tension headache | 1.2 | 0.5
Psychiatric Disorders
Insomnia | 12.3 | 6.1
Anxiety | 8.2 | 2.4
Initial insomnia | 4.3 | 2.8
Depressed mood | 3.9 | 1.4
Nervousness | 3.1 | 0.5
Restlessness | 3.1 | 0
Agitation | 2.2 | 0.5
Aggression | 1.7 | 0.5
Bruxism | 1.7 | 0.5
Depression | 1.7 | 0.9
Libido decreased | 1.7 | 0.5
Affect lability | 1.4 | 0.9
Confusional state | 1.2 | 0.5
Tension | 1.2 | 0.5
Respiratory, Thoracic and Mediastinal Disorders
Oropharyngeal pain | 1.7 | 1.4
Skin and Subcutaneous Tissue Disorders
Hyperhidrosis | 5.1 | 0.9
* Included doses up to 108 mg (1.5 times the maximum recommended dosage of RELEXXII).

Adverse Reactions Observed in Clinical Trials with Another Formulation of Methylphenidate Hydrochloride Extended-release Tablets

This section includes adverse reactions reported with use of another formulation of methylphenidate hydrochloride extended-release tablets in double-blind trials that do not meet the criteria specified for Table 4 or Table 5 and all adverse reactions reported by the other formulation of methylphenidate hydrochloride extended-release tablets-treated patients who participated in open-label and postmarketing clinical trials.

Blood and Lymphatic System Disorders: Leukopenia

Eye Disorders: Accommodation disorder, Dry eye

Vascular Disorders: Hot flush

Gastrointestinal Disorders: Abdominal discomfort, Abdominal pain, Diarrhea

General Disorders and Administrative Site Conditions: Asthenia, Fatigue, Feeling jittery, Thirst

Infections and Infestations: Sinusitis

Investigations: Alanine aminotransferase increased, Blood pressure increased, Cardiac murmur, Heart rate increased

Musculoskeletal and Connective Tissue Disorders: Muscle spasms

Nervous System Disorders: Lethargy, Psychomotor hyperactivity, Somnolence

Psychiatric Disorders: Anger, Hypervigilance, Mood altered, Mood swings, Panic attack, Sleep disorder, Tearfulness, Tic

Reproductive System and Breast Disorders: Erectile dysfunction

Respiratory, Thoracic and Mediastinal Disorders: Dyspnea

Skin and Subcutaneous Tissue Disorders: Rash, Rash macular

Vascular Disorders: Hypertension

Discontinuation Due to Adverse Reactions

Adverse reactions in the four placebo-controlled studies of pediatric patients (6 to 17 years) leading to discontinuation occurred in 2 patients (0.6%) treated with another formulation of methylphenidate hydrochloride extended-release tablets including depressed mood (1, 0.3%) and headache and insomnia (1, 0.3%), and 6 placebo patients (1.9%) including headache and insomnia (1, 0.3%), irritability (2, 0.6%), headache (1, 0.3%), psychomotor hyperactivity (1, 0.3%), and tic (1, 0.3%).

In the two placebo-controlled studies of adults, 25 patients (6.0%) treated with another formulation of methylphenidate hydrochloride extended-release tablets and 6 placebo patients (2.8%) discontinued due to an adverse reaction. Incidence of >0.5% in patients treated with another formulation of methylphenidate hydrochloride extended-release tablets included anxiety (1.7%), irritability (1.4%), blood pressure increased (1.0%), and nervousness (0.7%). In placebo patients, blood pressure increased and depressed mood had an incidence of >0.5% (0.9%).

In the eleven open-label studies of pediatric patients and adults, 266 patients (7.0%) treated with another formulation of methylphenidate hydrochloride extended-release tablets discontinued due to an adverse reaction. Incidence of >0.5% included insomnia (1.2%), irritability (0.8%), anxiety (0.7%), decreased appetite (0.7%), and tic (0.6%).

Tics

In a long-term uncontrolled study (n=432 pediatric patients 6 to 12 years), the cumulative incidence of new onset of tics was 9% after 27 months of treatment with another formulation of methylphenidate hydrochloride extended-release tablets.

In a second uncontrolled study (n=682 pediatric patients 6 to 12 years) the cumulative incidence of new-onset tics was 1% (9/682). The treatment period was up to 9 months with mean treatment duration of 7.2 months.

Blood Pressure and Heart Rate Increases

In the laboratory classroom clinical trials in pediatric patients 6 to 12 years (Studies 1 and 2), both another formulation of methylphenidate hydrochloride extended-release tablets once daily and methylphenidate three times daily increased resting pulse by an average of 2 to 6 bpm and produced average increases of systolic and diastolic blood pressure of roughly 1 to 4 mm Hg during the day, relative to placebo. In the placebo-controlled trial in pediatric patients 13 to 17 years (Study 4), mean increases from baseline in resting pulse rate were observed with another formulation of methylphenidate hydrochloride extended-release tablets and placebo at the end of the double-blind phase (5 and 3 beats/minute, respectively). Mean increases from baseline in blood pressure at the end of the double-blind phase for another formulation of methylphenidate hydrochloride extended-release tablets and placebo-treated patients were 0.7 and 0.7 mm Hg (systolic) and 2.6 and 1.4 mm Hg (diastolic), respectively. In one placebo-controlled study in adults (Study 6), dose-dependent mean increases of 3.9 to 9.8 bpm from baseline in standing pulse rate were observed with another formulation of methylphenidate hydrochloride extended-release tablets at the end of the double-blind treatment vs. an increase of 2.7 beats/minute with placebo. Mean changes from baseline in standing blood pressure at the end of double-blind treatment ranged from 0.1 to 2.2 mm Hg (systolic) and -0.7 to 2.2 mm Hg (diastolic) for another formulation of methylphenidate hydrochloride extended-release tablets and was 1.1 mm Hg (systolic) and -1.8 mm Hg (diastolic) for placebo. In a second placebo-controlled study in adults (Study 5), mean changes from baseline in resting pulse rate were observed for another formulation of methylphenidate hydrochloride extended-release tablets and placebo at the end of the double-blind treatment (3.6 and –1.6 beats/minute, respectively). Mean changes from baseline in blood pressure at the end of the double–blind treatment for another formulation of methylphenidate hydrochloride extended-release tablets and placebo-treated patients were –1.2 and –0.5 mm Hg (systolic) and 1.1 and 0.4 mm Hg (diastolic), respectively [see Warnings and Precautions (5.3)].

6.2 Postmarketing Experience

The following additional adverse reactions have been identified during post-approval use of another formulation of methylphenidate hydrochloride extended-release tablets. Because these reactions are reported voluntarily from a population of uncertain size, it is not always possible to reliably estimate their frequency or establish a causal relationship to drug exposure.

Blood and Lymphatic System Disorders: Pancytopenia, Thrombocytopenia, Thrombocytopenic purpura

Cardiac Disorders: Angina pectoris, Bradycardia, Extrasystoles, Supraventricular tachycardia, Ventricular extrasystoles

Eye Disorders: Diplopia, Increased intraocular pressure, Mydriasis, Visual impairment

General Disorders: Chest pain, Chest discomfort, Drug effect decreased, Hyperpyrexia, Therapeutic response decreased

Hepatobiliary Disorders: Hepatocellular injury, Acute hepatic failure

Immune System Disorders: Hypersensitivity reactions such as Angioedema, Anaphylactic reactions, Auricular swelling, Bullous conditions, Exfoliative conditions, Urticarias, Pruritus NEC, Rashes, Eruptions, and Exanthemas NEC

Investigations: Blood alkaline phosphatase increased, Blood bilirubin increased, Hepatic enzyme increased, Platelet count decreased, White blood cell count abnormal

Musculoskeletal, Connective Tissue and Bone Disorders: Arthralgia, Myalgia, Muscle twitching, Rhabdomyolysis

Nervous System Disorders: Convulsion, Grand mal convulsion, Dyskinesia, Serotonin syndrome in combination with serotonergic drugs, Motor and Verbal Tics

Psychiatric Disorders: Disorientation, Hallucination, Hallucination auditory, Hallucination visual, Mania, Logorrhea, Libido changes

Reproductive System and Breast Disorders: Priapism

Skin and Subcutaneous Tissue Disorders: Alopecia, Erythema

Vascular Disorders: Raynaud's phenomenon

7 DRUG INTERACTIONS

7.1 Clinically Important Drug Interactions

Table 6 presents clinically important drug interactions with RELEXXII.

Table 6: Drugs Having Clinically Important Interactions with RELEXXII

Monoamine Oxidase Inhibitors (MAOI)
Clinical Impact: | Concomitant use of MAOIs and CNS stimulants can cause hypertensive crisis. Potential outcomes include death, stroke, myocardial infarction, aortic dissection, ophthalmological complications, eclampsia, pulmonary edema, and renal failure [see Contraindications (4)].
Intervention: | Do not administer RELEXXII concomitantly with MAOIs or within 14 days after discontinuing MAOI treatment.
Antihypertensive Drugs
Clinical Impact: | RELEXXII may decrease the effectiveness of drugs used to treat hypertension [see Warnings and Precautions (5.3)].
Intervention: | Monitor blood pressure and adjust the dosage of the antihypertensive drug as needed.
Halogenated Anesthetics
Clinical Impact: | Concomitant use of halogenated anesthetics and RELEXXII may increase the risk of sudden blood pressure and heart rate increase during surgery.
Intervention: | Avoid use of RELEXXII in patients being treated with anesthetics on the day of surgery.
Risperidone
Clinical Impact: | Combined use of methylphenidate with risperidone when there is a change, whether an increase or decrease, in dosage of either or both medications, may increase the risk of extrapyramidal symptoms (EPS).
Intervention: | Monitor for signs of EPS.

8 USE IN SPECIFIC POPULATIONS

8.1 Pregnancy

Pregnancy Exposure Registry

There is a pregnancy exposure registry that monitors pregnancy outcomes in women exposed to ADHD medications, including RELEXXII, during pregnancy. Healthcare providers are encouraged to register patients by calling the National Pregnancy Registry for ADHD Medications at 1-866-961-2388.

Risk Summary

Published studies and post-marketing reports on methylphenidate use during pregnancy have not identified a drug-associated risk of major birth defects, miscarriage or adverse maternal or fetal outcomes. There are risks to the fetus associated with the use of central nervous system (CNS) stimulants during pregnancy (see Clinical Considerations).

No effects on morphological development were observed in development studies with oral administration of methylphenidate to pregnant rats at doses up to 4 times the maximum recommended human dose (MRHD) of 72 mg/day given to adults on a mg/m^2 basis. However, malformations were observed in rabbits at a dose 54 times the MRHD given to adults.

The estimated background risk of major birth defects and miscarriage for the indicated population is unknown. All pregnancies have a background risk of birth defect, loss, or other adverse outcomes. In the U.S. general population, the estimated background risk of major birth defects and miscarriage in clinically recognized pregnancies is 2 to 4% and 15 to 20%, respectively.

Clinical Considerations

Fetal/Neonatal Adverse Reactions

CNS stimulants, such as RELEXXII, can cause vasoconstriction and thereby decrease placental perfusion. No fetal and/or neonatal adverse reactions have been reported with the use of therapeutic doses of methylphenidate during pregnancy; however, premature delivery and low birth weight infants have been reported in amphetamine‑dependent mothers.

Data

Animal Data

In development studies conducted in rats and rabbits, methylphenidate was administered at doses up to 30 and 200 mg/kg/day, respectively. Methylphenidate has been shown to cause malformations in rabbits when given in doses of 200 mg/kg/day, which is approximately 54 times the MRHD on a mg/m^2 basis, respectively. A reproduction study in rats revealed no evidence of harm to the fetus at oral doses up to 30 mg/kg/day, approximately 4-fold the MRHD on a mg/m^2 basis.

8.2 Lactation

Risk Summary

Limited published literature, based on breast milk sampling from five mothers, reports that methylphenidate is present in human milk, which resulted in infant doses of 0.16% to 0.7% of the maternal weight-adjusted dosage and a milk/plasma ratio ranging between 1.1 and 2.7. There are no reports of adverse effects on the breastfed infant and no effects on milk production. However, long‑term neurodevelopmental effects on infants from CNS stimulant exposure are unknown. The developmental and health benefits of breastfeeding should be considered along with the mother’s clinical need for RELEXXII and any potential adverse effects on the breastfed infant from RELEXXII or from the underlying maternal condition.

Clinical Considerations

Monitor breastfeeding infants for adverse reactions, such as agitation, anorexia, and reduced weight gain.

8.4 Pediatric Use

The safety and effectiveness of RELEXXII have not been established in pediatric patients below the age of 6 years.

In studies evaluating extended-release methylphenidate products, patients 4 to <6 years of age had higher systemic methylphenidate exposures than those observed in older pediatric patients at the same dosage. Pediatric patients 4 to <6 years of age also had a higher incidence of adverse reactions, including weight loss.

The safety and effectiveness of RELEXXII for the treatment of ADHD have been established in pediatric patients 6 to 17 years.

Long Term Suppression of Growth

Growth should be monitored during treatment with stimulants, including RELEXXII. Pediatric patients who are not growing or gaining weight as expected may need to have their treatment interrupted [see Warnings and Precautions (5.7) and Adverse Reactions (6.1)].

Juvenile Animal Toxicity Data

In the study conducted in young rats, methylphenidate was administered orally at doses of up to 100 mg/kg/day for 9 weeks, starting early in the postnatal period (postnatal day 7) and continuing through sexual maturity (postnatal week 10). When these animals were tested as adults (postnatal weeks 13-14), decreased spontaneous locomotor activity was observed in males and females previously treated with 50 mg/kg/day (approximately 4 times the MRHD of 54 mg/day given to children on a mg/m^2 basis) or greater, and a deficit in the acquisition of a specific learning task was observed in females exposed to the highest dose (9 times the MRHD given to children on a mg/m^2 basis). The no effect level for juvenile neurobehavioral development in rats was 5 mg/kg/day (equal to the MRHD given to children on a mg/m^2 basis). The clinical significance of the long-term behavioral effects observed in rats is unknown.

8.5 Geriatric Use

RELEXXII has not been studied in patients greater than 65 years of age.

9 DRUG ABUSE AND DEPENDENCE

9.1 Controlled Substance

RELEXXII contains methylphenidate, a Schedule II controlled substance.

9.2 Abuse

RELEXXII has a high potential for abuse and misuse which can lead to the development of a substance use disorder, including addiction [see Warnings and Precautions (5.1)]. RELEXXII can be diverted for non-medical use into illicit channels or distribution.

Abuse is the intentional non-therapeutic use of a drug, even once, to achieve a desired psychological or physiological effect. Misuse is the intentional use, for therapeutic purposes, of a drug by an individual in a way other than prescribed by a healthcare provider or for whom it was not prescribed. Drug addiction is a cluster of behavioral, cognitive, and physiological phenomena that may include a strong desire to take the drug, difficulties in controlling drug use (e.g., continuing drug use despite harmful consequences, giving a higher priority to drug use than other activities and obligations), and possible tolerance or physical dependence.

Misuse and abuse of methylphenidate may cause increased heart rate, respiratory rate, or blood pressure; sweating; dilated pupils; hyperactivity; restlessness; insomnia; decreased appetite; loss of coordination; tremors; flushed skin; vomiting; and/or abdominal pain. Anxiety, psychosis, hostility, aggression, and suicidal or homicidal ideation have also been observed with CNS stimulants abuse and/or misuse. Misuse and abuse of CNS stimulants, including RELEXXII, can result in overdose and death [see Overdosage (10)], and this risk is increased with higher doses or unapproved methods of administration such as snorting or injection.

In two placebo-controlled human abuse potential studies, single oral doses of another formulation of methylphenidate hydrochloride extended-release tablets were compared to single oral doses of immediate-release methylphenidate (IR MPH) and placebo in subjects with a history of recreational stimulant use to assess relative abuse potential. For the purpose of this assessment, the response for each of the subjective measures was defined as the maximum effect within the first 8 hours after dose administration.

In one study (n=40), both the other formulation of methylphenidate hydrochloride extended-release tablets (108 mg, which is 1.5 times the maximum recommended dosage of methylphenidate hydrochloride extended-release tablets) and 60 mg IR MPH compared to placebo produced statistically significantly greater responses on the five subjective measures suggestive of abuse potential. In comparisons between the two active treatments, however, the other formulation of methylphenidate hydrochloride extended-release tablets (108 mg) produced variable responses on positive subjective measures that were either statistically indistinguishable from (Abuse Potential, Drug Liking, Amphetamine, and Morphine Benzedrine Group [Euphoria]) or statistically less than (Stimulation – Euphoria) responses produced by 60 mg IR MPH.

In another study (n=49), both doses of another formulation of methylphenidate hydrochloride extended-release tablets (54 mg and 108 mg) and both doses of IR MPH (50 mg and 90 mg) produced statistically significantly greater responses compared to placebo on the two primary scales used in the study (Drug Liking, Euphoria). When doses of the other methylphenidate hydrochloride extended-release tablets (54 mg and 108 mg) were compared to IR MPH (50 mg and 90 mg), respectively, methylphenidate hydrochloride extended-release tablets produced statistically significantly lower subjective responses on these two scales than IR MPH. Methylphenidate hydrochloride extended-release tablets (108 mg) produced responses that were statistically indistinguishable from the responses on these two scales produced by IR MPH (50 mg). Differences in subjective responses to the respective doses should be considered in the context that only 18% of the total amount of methylphenidate in RELEXXII is available for immediate release from the drug overcoat.

Although these findings reveal a relatively lower response to another formulation of methylphenidate hydrochloride extended-release tablets on subjective measures suggestive of abuse potential compared to IR MPH at roughly equivalent total MPH doses, the relevance of these findings to the abuse potential of RELEXXII in the community is unknown.

9.3 Dependence

Physical Dependence

RELEXXII may produce physical dependence. Physical dependence is a state that develops as a result of physiological adaptation in response to repeated drug use, manifested by withdrawal signs and symptoms after abrupt discontinuation or a significant dose reduction of a drug.

Withdrawal signs and symptoms after abrupt discontinuation or dose reduction following prolonged use of CNS stimulants including RELEXXII include dysphoric mood; depression; fatigue; vivid, unpleasant dreams; insomnia or hypersomnia; increased appetite; and psychomotor retardation or agitation.

Tolerance

RELEXXII may produce tolerance. Tolerance is a physiological state characterized by a reduced response to a drug after repeated administration (i.e., a higher dose of a drug is required to produce the same effect that was once obtained by a lower dose).

10 OVERDOSAGE

Clinical Effects of Overdose

Overdose of CNS stimulants is characterized by the following sympathomimetic effects:

- Cardiovascular effects including tachyarrhythmias, and hypertension or hypotension. Vasospasm, myocardial infarction, or aortic dissection may precipitate sudden cardiac death. Takotsubo cardiomyopathy may develop.
- CNS effects including psychomotor agitation, confusion, and hallucinations. Serotonin syndrome, seizures, cerebral vascular accidents, and coma may occur.
- Life-threatening hyperthermia (temperatures greater than 104°F) and rhabdomyolysis may develop.

Overdose Management

Consider the possibility of multiple drug ingestion. The pharmacokinetic profile of RELEXXII should be considered when treating patients with overdose. Because methylphenidate has a large volume of distribution and is rapidly metabolized, dialysis is not useful. Consider contacting the Poison Help line (1-800-222-1222) or a medical toxicologist for additional overdose management recommendations.

11 DESCRIPTION

RELEXXII contains methylphenidate, a CNS stimulant, present as methylphenidate hydrochloride salt. Chemically, methylphenidate hydrochloride is d,l (racemic) methyl α-phenyl-2-piperidineacetate hydrochloride. Its empirical formula is C14H19NO2•HCl. Its structural formula is:

Methylphenidate hydrochloride is a white, odorless crystalline powder. Its solutions are acid to litmus. It is freely soluble in water and in methanol, soluble in alcohol, and slightly soluble in chloroform and in acetone. It has a pKa of 8.71 (at 21.5°C). Its molecular weight is 269.77.

RELEXXII is for oral administration and is available in the following strengths: 18 mg, 27 mg, 36 mg, 45 mg, 54 mg, 63 mg, and 72 mg containing methylphenidate hydrochloride (equivalent to 15.6 mg, 23.4 mg, 31.1 mg, 38.9 mg, 46.7 mg, 54.5 mg, and 62.3 mg methylphenidate respectively).

RELEXXII contains the following inactive ingredients: cellulose acetate, colloidal silicon dioxide, ferrosoferric oxide, hypromellose, iron oxide black, lactose monohydrate, magnesium stearate, phosphoric acid, polyethylene glycol, polyethylene oxide, sodium chloride, succinic acid, titanium dioxide, triacetin.

RELEXXII also contains the following color additives:

27 mg: FD&C Yellow #6 Aluminum Lake, FD&C Blue #2 Aluminum Lake, FD&C Red #40 Aluminum Lake

45 mg: FD&C Red #40 Aluminum Lake

54 mg: FD&C Yellow #6 Aluminum Lake, FD&C Red #40 Aluminum Lake, FD&C Blue #2 Aluminum Lake

18 and 63 mg: iron oxide red, iron oxide yellow

72 mg: FD&C Blue #1 Aluminum Lake

System Components and Performance

RELEXXII uses osmotic pressure to deliver methylphenidate hydrochloride at a controlled rate. The system, which resembles a conventional tablet in appearance, comprises an osmotically active bilayer core surrounded by a semipermeable membrane with an immediate-release drug overcoat. The bilayer core is composed of a drug layer containing the drug and excipients, and a push layer containing osmotically active components. There is a precision-laser drilled orifice on the drug-layer end of the tablet. In an aqueous environment, such as the gastrointestinal tract, the drug overcoat dissolves within one hour, providing an initial dose of methylphenidate. Water permeates through the membrane into the tablet core. As the osmotically active polymer excipients expand, methylphenidate is released through the orifice. The membrane controls the rate at which water enters the tablet core, which in turn controls drug delivery. Furthermore, the drug release rate from the system increases with time over a period of 6 to 7 hours due to the drug-concentration gradient incorporated into the two drug layers of core of RELEXXII. The biologically inert components of the tablet remain intact during gastrointestinal transit and are eliminated in the stool as a tablet shell along with insoluble core components. It is possible that RELEXXII may be visible on abdominal x-rays under certain circumstances, especially when digital enhancing techniques are utilized.

12 CLINICAL PHARMACOLOGY

12.1 Mechanism of Action

Methylphenidate HCl is a CNS stimulant. The mode of therapeutic action in ADHD is not known.

12.2 Pharmacodynamics

Methylphenidate is a racemic mixture comprised of the d- and l-threo entantiomers. The d-threo enantiomer is more pharmacologically active than the l-threo enantiomer. Methylphenidate blocks the reuptake of norepinephrine and dopamine into the presynaptic neuron and increase the release of these monoamines into the extraneuronal space.

12.3 Pharmacokinetics

In a relative bioavailability study in healthy adults under fasted conditions, plasma exposures of 72 mg RELEXXII and 72 mg (2 x 36 mg) methylphenidate extended-release tablets were compared. The peak plasma concentration (Cmax) of RELEXXII and methylphenidate extended-release tablets is 19.7 ng/mL and 19.3 ng/mL, respectively. The area under the plasma concentration-time curve (AUC0-inf) of RELEXXII and methylphenidate extended-release tablets is 206.1 ng∙h/mL and 200.9 ng∙h/mL, respectively.

Absorption

Methylphenidate is readily absorbed. Following oral administration of RELEXXII plasma methylphenidate concentrations increase rapidly, reaching an initial maximum at about 1.5 hour, followed by gradual ascending concentrations over the next 5 to 6 hours, after which a gradual decrease begins. Mean time to reach peak plasma concentrations of RELEXXII occurs at 5.5 hours.

Methylphenidate hydrochloride extended-release tablets once daily minimizes the fluctuations between peak and trough concentrations associated with immediate-release methylphenidate three times daily. Figure 1 displays mean plasma exposures of methylphenidate hydrochloride extended-release tablets once daily and methylphenidate three times daily (administered every 4 hours) in adults.

Figure 1: Mean Methylphenidate Plasma Concentration-Time Profiles

The mean single-dose pharmacokinetic parameters in 36 healthy adults following the administration of methylphenidate hydrochloride extended-release tablets 18 mg once daily and methylphenidate 5 mg three times daily are summarized in Table 7.

Table 7: Methylphenidate Pharmacokinetic Parameters (Mean ± SD) After Single Dose in Healthy Adults

Parameters | Methylphenidate Hydrochloride Extended-release Tablets (18 mg once daily) (n=36) | Methylphenidate (5 mg three times daily) (n=35)
Cmax (ng/mL) | 3.7 ± 1.0 | 4.2 ± 1.0
Tmax (h) | 6.8 ± 1.8 | 6.5 ± 1.8
AUCinf (ng∙h/mL) | 41.8 ± 13.9 | 38.0 ± 11.0
t1/2 (h) | 3.5 ± 0.4 | 3.0 ± 0.5

The pharmacokinetics of methylphenidate hydrochloride extended-release tablets were evaluated in healthy adults following single- and multiple-dose administration (steady state) of doses up to 144 mg per day (2 times the maximum recommended daily dosage of methylphenidate hydrochloride extended-release tablets). The mean half-life was about 3.6 hours. No differences in the pharmacokinetics of methylphenidate hydrochloride extended-release tablets were noted following single and repeated once-daily dosing, indicating no significant drug accumulation. The AUC and t1/2 following repeated once-daily dosing are similar to those following the first dose of methylphenidate hydrochloride extended-release tablets in a dose range of 18 mg to 144 mg.

Effect of Food

There were no differences in either the pharmacokinetics or the pharmacodynamic performance of methylphenidate hydrochloride extended-release tablets when administered after a high-fat breakfast. There is no evidence of dose dumping in the presence or absence of food.

Effect of Alcohol

In-vitro studies were conducted to explore the effect of alcohol on the release characteristics of methylphenidate from RELEXXII. At alcohol concentrations up to 40%, there was no increased release of methylphenidate in the first two hours.

Dose Proportionality

Following administration methylphenidate hydrochloride extended-release tablets in single doses of 18 mg, 36 mg, and 54 mg per day to healthy adults, Cmax and AUC (0–inf) of d-methylphenidate were proportional to dose, whereas l-methylphenidate Cmax and AUC (0–inf) increased disproportionately with respect to dose. Following administration of methylphenidate hydrochloride extended-release tablets, plasma concentrations of the l-isomer were approximately 1/40 the plasma concentrations of the d-isomer.

In healthy adults, single and multiple dosing of once-daily methylphenidate hydrochloride extended-release tablets doses from 54 mg to 144 mg per day resulted in linear and dose-proportional increases in Cmax and AUCinf for total methylphenidate (MPH) and its major metabolite, α-phenyl-piperidine acetic acid (PPAA). There was no time dependency in the pharmacokinetics of methylphenidate. The ratio of metabolite (PPAA) to parent drug (MPH) was constant across doses from 54 mg to 144 mg per day, both after single dose and upon multiple dosing.

In a multiple-dose study in ADHD with pediatric patients 13 to 16 years administered their prescribed dose (18 mg to 72 mg per day) of methylphenidate hydrochloride extended-release tablets, mean Cmax and AUCTAU of d- and total methylphenidate increased proportionally with respect to dose.

Distribution

Plasma methylphenidate concentrations in adults and pediatric patients 13 to 17 years decline biexponentially following oral administration. The half-life of methylphenidate in adults and adolescents following oral administration of methylphenidate hydrochloride extended-release tablets was approximately 3.5 hours.

Elimination

Metabolism

In humans, methylphenidate is metabolized primarily by de-esterification to PPAA, which has little or no pharmacologic activity. In adults the metabolism of methylphenidate hydrochloride extended-release tablets once daily as evaluated by metabolism to PPAA is similar to that of methylphenidate three times daily. The metabolism of single and repeated once-daily doses of methylphenidate hydrochloride extended-release tablets is similar.

Excretion

After oral dosing of radiolabeled methylphenidate in humans, about 90% of the radioactivity was recovered in urine. The main urinary metabolite was PPAA, accounting for approximately 80% of the dose.

Specific Populations

Male and Female Patients

In healthy adults, the mean dose-adjusted AUC (0–inf) values for methylphenidate hydrochloride extended-release tablets were 36.7 ng∙h/mL in men and 37.1 ng∙h/mL in women, with no differences noted between the two groups.

Racial or Ethnic Groups

In adults receiving methylphenidate hydrochloride extended-release tablets, dose-adjusted AUC (0–inf) was consistent across ethnic groups; however, the sample size may have been insufficient to detect ethnic variations in pharmacokinetics.

Pediatric Patients

Increase in age resulted in increased apparent oral clearance (CL/F) (58% increase in pediatric patients 13 to 17 years compared to pediatric patients 6 to 12 years). Some of these differences could be explained by body-weight differences among these populations. This suggests that subjects with higher body weight may have lower exposures of total methylphenidate at similar doses.

The pharmacokinetics of methylphenidate hydrochloride extended-release tablets have not been studied in pediatric patients less than 6 years of age.

Patients with Renal Impairment

There is no experience with the use of methylphenidate hydrochloride extended-release tablets in patients with renal insufficiency. After oral administration of radiolabeled methylphenidate in humans, methylphenidate was extensively metabolized and approximately 80% of the radioactivity was excreted in the urine in the form of PPAA. Since renal clearance is not an important route of methylphenidate clearance, renal insufficiency is expected to have little effect on the pharmacokinetics of methylphenidate hydrochloride extended-release tablets.

Patients with Hepatic Impairment

There is no experience with the use of methylphenidate hydrochloride extended-release tablets in patients with hepatic insufficiency.

13 NONCLINICAL TOXICOLOGY

13.1 Carcinogenesis, Mutagenesis, and Impairment of Fertility

Carcinogenesis

In a lifetime carcinogenicity study carried out in B6C3F1 mice, methylphenidate caused an increase in hepatocellular adenomas and, in males only, an increase in hepatoblastomas at a daily dose of approximately 60 mg/kg/day. This dose is approximately 4 times the MRHD of methylphenidate hydrochloride extended-release tablets on a mg/m^2 basis, respectively. Hepatoblastoma is a relatively rare rodent malignant tumor type. There was no increase in total malignant hepatic tumors. The mouse strain used is sensitive to the development of hepatic tumors, and the significance of these results to humans is unknown.

Methylphenidate did not cause any increases in tumors in a lifetime carcinogenicity study carried out in F344 rats; the highest dose used was approximately 45 mg/kg/day, which is approximately 6 times the MRHD of methylphenidate hydrochloride extended-release tablets on a mg/m^2 basis, respectively.

In a 24-week carcinogenicity study in the transgenic mouse strain p53+/-, which is sensitive to genotoxic carcinogens, there was no evidence of carcinogenicity. Male and female mice were fed diets containing the same concentration of methylphenidate as in the lifetime carcinogenicity study; the high-dose groups were exposed to 60 to 74 mg/kg/day of methylphenidate.

Mutagenesis

Methylphenidate was not mutagenic in the in vitro Ames reverse mutation assay or the in vitro mouse lymphoma cell forward mutation assay. Sister chromatid exchanges and chromosome aberrations were increased, indicative of a weak clastogenic response, in an in vitro assay in cultured Chinese Hamster Ovary cells. Methylphenidate was negative in vivo in males and females in the mouse bone marrow micronucleus assay.

Impairment of Fertility

Methylphenidate did not impair fertility in male or female mice that were fed diets containing the drug in an 18-week Continuous Breeding study. The study was conducted at doses up to 160 mg/kg/day, approximately 11-fold the MRHD of methylphenidate hydrochloride extended-release tablets on a mg/m^2 basis, respectively.

14 CLINICAL STUDIES

The efficacy of RELEXXII for the treatment of Attention Deficit Hyperactivity Disorder (ADHD) in pediatric patients (6 to 17 years) and adult patients is based upon adequate and well-controlled studies of another formulation of methylphenidate hydrochloride extended-release tablets (referred to as “methylphenidate hydrochloride extended-release tablets” in the section below). The results of these adequate and well-controlled studies are presented below.

Methylphenidate hydrochloride extended-release tablets was demonstrated to be effective in the treatment of Attention Deficit Hyperactivity Disorder (ADHD) in four randomized, double-blind, placebo-controlled studies in pediatric patients 6 to 17 years and two double-blind placebo-controlled studies in adults who met the Diagnostic and Statistical Manual 4th edition (DSM-IV) criteria for ADHD.

Pediatric Patients 6 to 12 Years

Three double-blind, active- and placebo-controlled studies were conducted in 416 pediatric patients 6 to 12 years. The controlled studies compared methylphenidate hydrochloride extended-release tablets given once daily (18 mg, 36 mg, or 54 mg), methylphenidate given three times daily over 12 hours (15 mg, 30 mg, or 45 mg total daily dose), and placebo in two single-center, 3-week crossover studies (Studies 1 and 2) and in a multicenter, 4-week, parallel-group comparison (Study 3). The primary comparison of interest in all three trials was methylphenidate hydrochloride extended-release tablets versus placebo.

Symptoms of ADHD were evaluated by community schoolteachers using the Inattention/Overactivity with Aggression (IOWA) Conners scale. Statistically significant reduction in the Inattention/Overactivity subscale versus placebo was shown consistently across all three controlled studies for methylphenidate hydrochloride extended-release tablets. Studies 1 and 2 involved a 3-way crossover of 1 week per treatment arm. Study 3 involved 4 weeks of parallel-group treatments with a Last Observation Carried Forward analysis at Week 4.

The scores for methylphenidate hydrochloride extended-release tablets and placebo for the three studies are presented in Figure 2. Error bars represent the mean plus standard error of the mean.

Figure 2: Mean Community School Teacher IOWA Conners Inattention/Overactivity Scores with Methylphenidate Hydrochloride Extended-Release Tablets Once Daily (18 mg, 36 mg, or 54 mg) and Placebo (Studies 1, 2, and 3)

In Studies 1 and 2, symptoms of ADHD were evaluated by laboratory schoolteachers using the Swanson, Kotkin, Agler, M-Fynn, and Pelham (SKAMP) laboratory school rating scale. The combined results from these two studies demonstrated statistically significant improvements in attention and behavior in patients treated with methylphenidate hydrochloride extended-release tablets versus placebo that were maintained through 12 hours after dosing. Figure 3 presents the laboratory schoolteacher SKAMP ratings for methylphenidate hydrochloride extended-release tablets and placebo.

Figure 3: Laboratory School Teacher SKAMP Ratings: Mean (SEM) of Combined Attention (Studies 1 and 2)

Pediatric Patients 13 to 17 years

In a randomized, double-blind, multicenter, placebo-controlled trial (Study 4) involving 177 patients, methylphenidate hydrochloride extended-release tablets was demonstrated to be effective in the treatment of ADHD in pediatric patients aged 13 to 18 years at doses up to 72 mg once daily (1.4 mg/kg/day). Of 220 patients who entered an open 4-week titration phase, 177 were titrated to an individualized dose (maximum of 72 mg once daily) based on meeting specific improvement criteria on the ADHD Rating Scale and the Global Assessment of Effectiveness with acceptable tolerability. Patients who met these criteria were then randomized to receive either their individualized dose of methylphenidate hydrochloride extended-release tablets (18 mg to 72 mg once daily, n=87) or placebo (n=90) during a two-week double-blind phase. At the end of this phase, mean scores for the investigator rating on the ADHD Rating Scale demonstrated that methylphenidate hydrochloride extended-release tablets was statistically significantly superior to placebo.

Adults

Two double-blind, placebo-controlled studies were conducted in 627 adults aged 18 to 65 years. The controlled studies compared methylphenidate hydrochloride extended-release tablets administered once daily and placebo in a multicenter, parallel-group, 7-week dose-titration study (Study 5) (36 mg to 108 mg once daily) and in a multicenter, parallel-group, 5-week, fixed-dose study (Study 6) (18 mg, 36 mg, and 72 mg once daily).

Study 5 demonstrated the effectiveness of methylphenidate hydrochloride extended-release tablets in the treatment of ADHD in adults aged 18 to 65 years at doses from 36 mg once daily to 108 mg once daily based on the change from baseline to final study visit on the Adult ADHD Investigator Rating Scale (AISRS). Of 226 patients who entered the 7-week trial, 110 were randomized to methylphenidate hydrochloride extended-release tablets and 116 were randomized to placebo. Treatment was initiated at 36 mg once daily and patients continued with incremental increases of 18 mg once daily (36 mg to 108 mg once daily) based on meeting specific improvement criteria with acceptable tolerability. At the final study visit, mean change scores (LS Mean, SEM) for the investigator rating on the AISRS demonstrated methylphenidate hydrochloride extended-release tablets was statistically significantly superior to placebo.

Study 6 was a multicenter, double-blind, randomized, placebo-controlled, parallel-group, dose-response study (5-week duration) with 3 fixed-dose groups (18 mg, 36 mg, and 72 mg). Patients were randomized to receive methylphenidate hydrochloride extended-release tablets administered at doses of 18 mg (n=101), 36 mg (n=102), 72 mg once daily (n=102), or placebo (n=96). All three doses of methylphenidate hydrochloride extended-release tablets were statistically significantly more effective than placebo in improving CAARS (Conners' Adult ADHD Rating Scale) total scores at double-blind end point in adult subjects with ADHD.

16 HOW SUPPLIED/STORAGE AND HANDLING

How Supplied

RELEXXII® (methylphenidate hydrochloride extended-release tablets) are available as:

- 18 mg yellow tablets with "TL706" imprinted in black ink
  - NDC 68025-095-30 in 30-count bottle
  - NDC 68025-095-10 in 100-count bottle
- 27 mg gray tablets with "TL707" imprinted in black ink
  - NDC 68025-096-30 in 30-count bottle
  - NDC 68025-096-10 in 100-count bottle
- 36 mg white tablets with "TL708" imprinted in black ink
  - NDC 68025-097-30 in 30-count bottle
  - NDC 68025-097-10 in 100-count bottle
- 45 mg pink tablets with "TL711" imprinted in black ink
  - NDC 68025-088-30 in 30-count bottle
- 54 mg pink tablets with "TL709" imprinted in black ink
  - NDC 68025-098-30 in 30-count bottle
  - NDC 68025-098-10 in 100-count bottle
- 63 mg orange tablets with "TL700" imprinted in black ink
  - NDC 68025-089-30 in 30-count bottle
- 72 mg blue tablets with "TL710" imprinted in black ink
  - NDC 68025-084-30 in 30-count bottle

Storage and Handling

Store at 20°C to 25°C (68°F to 77°F); excursions permitted to 15°C to 30°C (59°F to 86°F) [see USP Controlled Room Temperature]. Protect from humidity.

17 PATIENT COUNSELING INFORMATION

Advise the patient to read the FDA-approved patient labeling (Medication Guide).

Abuse, Misuse, and Addiction

Educate patients and their families about the risks of abuse, misuse, and addiction of RELEXXII, which can lead to overdose and death, and proper disposal of any unused drug [see Warnings and Precautions (5.1), Drug Abuse and Dependence (9.2), and Overdosage (10)]. Advise patients to store RELEXXII in a safe place, preferably locked, and instruct patients to not give RELEXXII to anyone else.

Administration Instructions

Instruct patients to swallow RELEXXII whole with the aid of liquids, and not to chew, divide, or crush the tablets. Advise patients that the medication is contained within a nonabsorbable shell designed to release the drug at a controlled rate. The tablet shell, along with insoluble core components, is eliminated from the body; advise patients not to be concerned if they occasionally notice in their stool something that looks like a tablet [see Dosage and Administration (2.2), Warnings and Precautions (5.8)].

Risks to Patients with Serious Cardiac Disease

Advise patients that there are potential risks to patients with serious cardiac disease, including sudden death with RELEXXII use. Instruct patients to contact a healthcare provider immediately if they develop symptoms such as exertional chest pain, unexplained syncope, or other symptoms suggestive of cardiac disease [see Warnings and Precautions (5.2)].

Increased Blood Pressure and Heart Rate

Advise patients and their caregivers that RELEXXII can cause elevations of their blood pressure and pulse rate [see Warnings and Precautions (5.3)].

Psychiatric Adverse Reactions

Advise patients and their caregivers that RELEXXII, at recommended doses, can cause psychotic or manic symptoms, even in patients without prior history of psychotic symptoms or mania [see Warnings and Precautions (5.4)].

Priapism

Advise patients, caregivers, and family members of the possibility of painful or prolonged penile erections (priapism). Instruct the patient to seek immediate medical attention in the event of priapism [see Warnings and Precautions (5.5)].

Circulation Problems in Fingers and Toes [Peripheral Vasculopathy, including Raynaud’s Phenomenon] [see Warnings and Precautions (5.6)].

- Instruct patients beginning treatment with RELEXXII about the risk of peripheral vasculopathy, including Raynaud’s phenomenon, and associated signs and symptoms: fingers or toes may feel numb, cool, painful, and/or may change color from pale, to blue, to red.
- Instruct patients to report to their healthcare provider any new numbness, pain, skin color change, or sensitivity to temperature in fingers or toes.
- Instruct patients to call their physician immediately with any signs of unexplained wounds appearing on fingers or toes while taking RELEXXII.
- Further clinical evaluation (e.g., rheumatology referral) may be appropriate for certain patients.

Long-Term Suppression of Growth in Pediatric Patients

Advise patients, families and caregivers that RELEXXII may cause slowing of growth and weight loss [see Warnings and Precautions (5.7)].

Increased Intraocular Pressure (IOP) and Glaucoma

Advise patients that IOP and glaucoma may occur during treatment with RELEXXII [see Warnings and Precautions (5.10)].

Motor and Verbal Tics, and Worsening of Tourette’s Syndrome

Advise patients that motor and verbal tics and worsening of Tourette’s Syndrome may occur during treatment with RELEXXII. Instruct patients to notify their healthcare provider if emergence of new tics or worsening of tics or Tourette’s syndrome occurs [see Warnings and Precautions (5.11].

Pregnancy Registry

Advise patients that there is a pregnancy exposure registry that monitors pregnancy outcomes in women exposed to RELEXXII during pregnancy [see Use in Specific Populations (8.1)].

Manufactured for:

Vertical Pharmaceuticals, LLC

Alpharetta, GA 30005

1-800-444-5164

www.verticalpharma.com

200438-8

Patent numbers:

US 9,855,258

US 9,827,234

US 9,707,217

US 10,265,308

US 10,695,336

MEDICATION GUIDE

RELEXXII® (RE-LEX-EE)

(methylphenidate hydrochloride extended-release tablets)

for oral use, CII

What is the most important information I should know about RELEXXII?

RELEXXII may cause serious side effects, including:

- Abuse, misuse, and addiction. RELEXXII has a high chance for abuse and misuse and may lead to substance use problems, including addiction. Misuse and abuse of RELEXXII, other methylphenidate containing medicines, and amphetamine containing medicines, can lead to overdose and death. The risk of overdose and death is increased with higher doses of RELEXXII or when it is used in ways that are not approved, such as snorting or injection.

- Your healthcare provider should check you or your child’s risk for abuse, misuse, and addiction before starting treatment with RELEXXII and will monitor you or your child during treatment.
- RELEXXII may lead to physical dependence after prolonged use, even if taken as directed by your healthcare provider.
- Do not give RELEXXII to anyone else. See “What is RELEXXII?” for more information.
- Keep RELEXXII in a safe place and properly dispose of any unused medicine. See “How should I store RELEXXII?”
- Tell your healthcare provider if you or your child have ever abused or been dependent on alcohol, prescription medicines, or street drugs.

- Risks for people with serious heart disease. Sudden death has happened in people who have heart defects or other serious heart disease.
  Your healthcare provider should check you or your child carefully for heart problems before starting treatment with RELEXXII. Tell your healthcare provider if you or your child have any heart problems, heart disease, or heart defects.
  Call your healthcare provider or go to the nearest hospital emergency room right away if you or your child have any signs of heart problems such as chest pain, shortness of breath, or fainting during treatment with RELEXXII.
- Increased blood pressure and heart rate.

Your healthcare provider should check your or your child's blood pressure and heart rate regularly during treatment with RELEXXII.

- Mental (psychiatric) problems, including:

- new or worse behavior and thought problems

- new or worse bipolar illness

- new psychotic symptoms (such as hearing voices, or seeing or believing things that are not real) or new manic symptoms

Tell your healthcare provider about any mental problems you or your child have, or about a family history of suicide, bipolar illness, or depression.

Call your healthcare provider right away if you or your child have any new or worsening mental symptoms or problems during treatment with RELEXXII, especially hearing voices, seeing or believing things that are not real, or new manic symptoms.

What is RELEXXII?

RELEXXII is a central nervous system (CNS) stimulant prescription medicine used for the treatment of Attention Deficit Hyperactivity Disorder (ADHD) in adults less than 65 years of age and children 6 years of age and older. RELEXXII may help increase attention and decrease impulsiveness and hyperactivity in people with ADHD.

RELEXXII is not recommended for use in children under 6 years of age with ADHD.

RELEXXII has not been studied in adults older than 65 years of age.

RELEXXII is a federally controlled substance (CII) because it contains methylphenidate that can be a target for people who abuse prescription medicines or street drugs. Keep RELEXXII in a safe place to protect it from theft. Never give your RELEXXII to anyone else because it may cause death or harm them. Selling or giving away RELEXXII may harm others and is against the law.

Do not take RELEXXII if: you or your child are:

- allergic to methylphenidate or any of the ingredients in RELEXXII. See the end of this Medication Guide for a complete list of ingredients in RELEXXII.
- taking, or have stopped taking within the past 14 days, a medicine called a monoamine oxidase inhibitor (MAOI).

Before taking RELEXXII tell your healthcare provider about all your medical conditions, including if you or your child:

- have heart problems, heart disease, heart defects, or high blood pressure
- have mental problems including psychosis, mania, bipolar illness, or depression, or a family history of suicide, bipolar illness, or depression
- have circulation problems in fingers and toes
- have eye problems, including increased pressure in your eye, glaucoma, or problems with your close-up vision (farsightedness)
- have or had repeated movements or sounds (tics) or Tourette’s syndrome, or have a family history of tics or Tourette’s syndrome
- are pregnant or plan to become pregnant. It is not known if RELEXXII will harm the unborn baby.
  - Pregnancy Exposure Registry: There is a pregnancy registry for women who are exposed to RELEXXII during pregnancy. The purpose of the registry is to collect information about the health of women exposed to RELEXXII and their baby. If you or your child becomes pregnant during treatment with RELEXXII, talk to your healthcare provider about registering with the National Pregnancy Registry for Psychostimulants at 1-866-961-2388.

- are breastfeeding or plan to breastfeed. RELEXXII passes into breast milk. Talk to your healthcare provider about the best way to feed the baby during treatment with RELEXXII.

Tell your healthcare provider about all of the medicines that you or your child take, including prescription and over-the-counter medicines, vitamins, and herbal supplements.

RELEXXII and some medicines may interact with each other and cause serious side effects. Sometimes the doses of other medicines will need to be changed during treatment with RELEXXII. Your healthcare provider will decide whether RELEXXII can be taken with other medicines.

Especially tell your healthcare provider if you or your child takes:

- blood pressure medicines (anti-hypertensive)

Know the medicines that you take or your child take. Keep a list of your medicines with you to show your healthcare provider and pharmacist. Do not start any new medicine during treatment with RELEXXII without first talking to your healthcare provider.

How should RELEXXII be taken?

- Take RELEXXII exactly as prescribed by your healthcare provider.
- Your healthcare provider may change the dose or tell you to stop taking RELEXXII if needed.
- Take RELEXXII 1 time each day in the morning with or without food.
- Swallow RELEXXII whole with water or other liquids. Do not chew, crush, or divide the tablets. Tell your healthcare provider if you or your child cannot swallow RELEXXII whole. A different medicine may need to be prescribed.
- RELEXXII does not dissolve completely in the body after all the medicine has been released. You or your child may sometimes notice the empty tablet in a bowel movement. This is normal.

If you or your child take too much RELEXXII, call your healthcare provider or Poison Help line at 1-800-222-1222 or go to the nearest hospital emergency room right away.

What are the possible side effects of RELEXXII?

RELEXXII may cause serious side effects, including:

- See "What is the most important information I should know about RELEXXII?"
- Painful and prolonged erections (priapism). Priapism that may require surgery has happened in males who take products that contain methylphenidate. If you or your child develop priapism, get medical help right away.
- Circulation problems in fingers and toes (peripheral vasculopathy, including Raynaud’s phenomenon): Signs and symptoms may include:
  - fingers or toes may feel numb, cool, painful
  - fingers or toes may change color from pale, to blue, to red
  Tell your healthcare provider if you or your child have numbness, pain, skin color change, or sensitivity to temperature in your fingers or toes, or if you or your child have any signs of unexplained wounds appearing on fingers or toes during treatment with RELEXXII.
- Slowing of growth (height and weight) in children. Children should have their height and weight checked often during treatment with RELEXXII. RELEXXII treatment may be stopped if your child is not growing or gaining weight.
- Possible blockage of the intestine. Because the RELEXXII tablet does not change in shape in the intestines (GI tract), RELEXXII should not be taken by people with severe intestinal problems (preexisting severe gastrointestinal narrowing).
- Eye problems (increased pressure in the eye and glaucoma). Call your healthcare provider right away if you or your child develop changes in your vision or eye pain, swelling, or redness.
- New or worsening tics or worsening Tourette’s syndrome. Tell your healthcare provider if you or your child get any new or worsening tics or worsening Tourette’s syndrome during treatment with RELEXXII.

The most common side effects of RELEXXII in adults include:

• decreased appetite • headache

• dry mouth • nausea

• trouble sleeping (insomnia) • anxiety

• dizziness • weight loss

• irritability • increased sweating

The most common side effects of RELEXXII in children 6 to 17 years of age was stomach pain.

These are not all the possible side effects of RELEXXII.

Call your doctor for medical advice about side effects. You may report side effects to FDA at 1-800-FDA-1088.

How should I store RELEXXII?

- Store RELEXXII at room temperature between 68°F to 77°F (20°C to 25°C).
- Store RELEXXII in a safe place, like a locked cabinet. Protect from light and moisture.
- Dispose of remaining, unused, or expired RELEXXII by a medicine take-back program at a U.S. Drug Enforcement Administration (DEA) authorized collection site. If no take-back program or DEA authorized collector is available, mix RELEXXII with an undesirable, nontoxic substance such as dirt, cat litter, or used coffee grounds to make it less appealing to children and pets. Place the mixture in a container such as a sealed plastic bag and throw away RELEXXII in the household trash. Visit www.fda.gov/drugdisposal for additional information on disposal of unused medicines.

Keep RELEXXII and all medicines out of the reach of children.

General information about the safe and effective use of RELEXXII.
Medicines are sometimes prescribed for purposes other than those listed in a Medication Guide. Do not use RELEXXII for a condition for which it was not prescribed. Do not give RELEXXII to other people, even if they have the same symptoms that you have. It may harm them and it is against the law. You can ask your healthcare provider or pharmacist for information about RELEXXII that is written for healthcare professionals.

What are the ingredients in RELEXXII?

Active Ingredient: methylphenidate hydrochloride

Inactive Ingredients: cellulose acetate, colloidal silicon dioxide, ferrosoferric oxide, hypromellose, iron oxide black, lactose monohydrate, magnesium stearate, phosphoric acid, polyethylene glycol, polyethylene oxide, sodium chloride, succinic acid, titanium dioxide, and triacetin.

27 mg tablets contain: FD&C Yellow #6 Aluminum Lake, FD&C Blue #2 Aluminum Lake, FD&C Red #40 Aluminum Lake

45 mg tablets contain: FD&C Red #40 Aluminum Lake

54 mg tablets contain: FD&C Yellow #6 Aluminum Lake, FD&C Red #40 Aluminum Lake, FD&C Blue #2 Aluminum Lake

18 and 63 mg tablets contain: iron oxide red, iron oxide yellow

72 mg tablets contain: FD&C Blue #1 Aluminum Lake

Manufactured for:

Vertical Pharmaceuticals, LLC

Alpharetta, GA 30005

For more information, go to www.verticalpharma.com or call 1-800-444-5164

200438-8

This Medication Guide has been approved by the U.S. Food and Drug Administration. Revised: 09/2025

PRINCIPAL DISPLAY PANEL

RELEXXII® 18 mg 100 count Bottle Label

NDC 68025-095-10

PRINCIPAL DISPLAY PANEL

RELEXXII® 18 mg 30 count Bottle Label

NDC 68025-095-30

PRINCIPAL DISPLAY PANEL

RELEXXII® 27 mg 100 count Bottle Label

NDC 68025-096-10

PRINCIPAL DISPLAY PANEL

RELEXXII® 27 mg 30 count Bottle Label

NDC 68025-096-30

PRINCIPAL DISPLAY PANEL

RELEXXII® 36 mg 100 count Bottle Label

NDC 68025-097-10

PRINCIPLE DISPLAY PANEL

RELEXXII® 36 mg 30 count Bottle Label

NDC 68025-097-30

PRINCIPAL DISPLAY PANEL

RELEXXII® 45 mg 30 count Bottle Label

NDC 68025-088-30

PRINCIPAL DISPLAY PANEL

RELEXXII® 54 mg 100 count Bottle Label

NDC 68025-098-10

PRINCIPLE DISPLAY PANEL

RELEXXII® 54 mg 30 count Bottle Label

NDC 68025-098-30

PRINCIPAL DISPLAY PANEL

RELEXXII® 63 mg 30 count Bottle Label

NDC 68025-089-30

PRINCIPAL DISPLAY PANEL

RELEXXII® 72 mg 30 count Bottle Label

NDC 68025-084-30